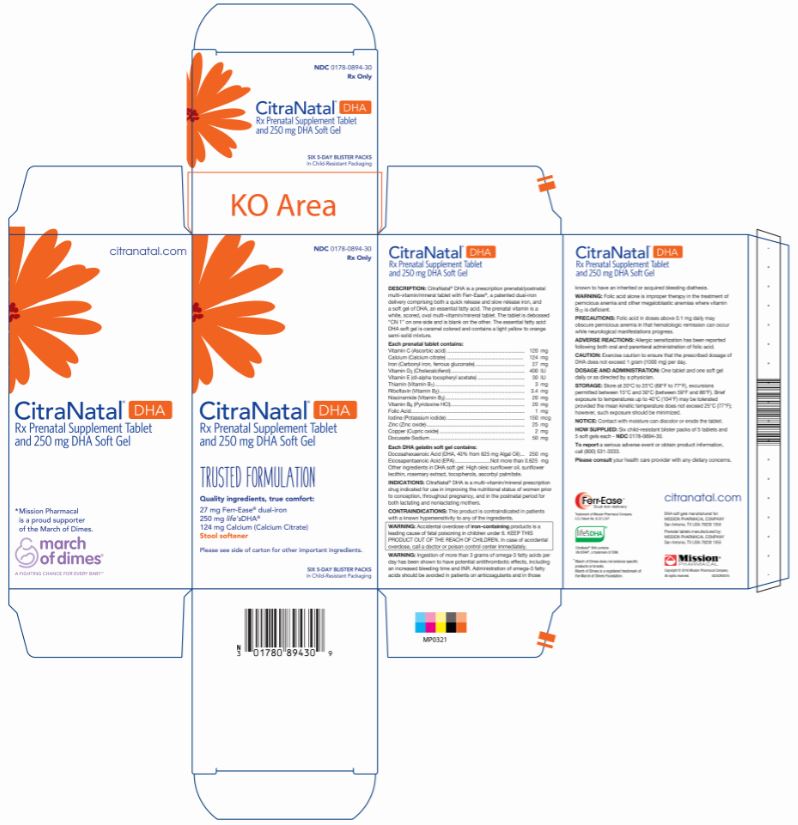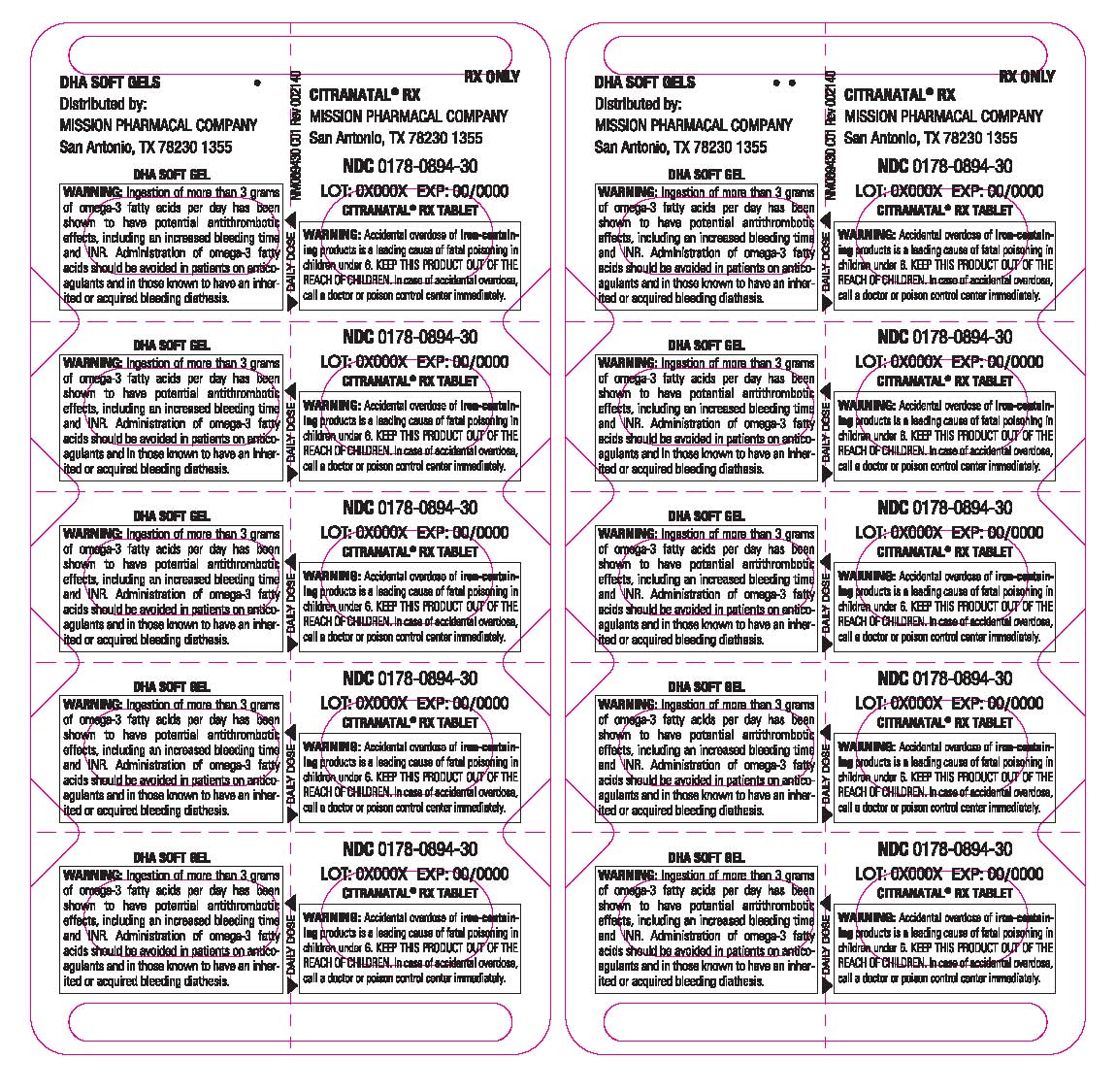 DRUG LABEL: CitraNatal DHA
NDC: 0178-0894 | Form: KIT | Route: ORAL
Manufacturer: Mission Pharmacal Company
Category: prescription | Type: HUMAN PRESCRIPTION DRUG LABEL
Date: 20200728

ACTIVE INGREDIENTS: ASCORBIC ACID 120 mg/1 1; VITAMIN D 400 [iU]/1 1; IRON 27 mg/1 1; .ALPHA.-TOCOPHEROL ACETATE 30 [iU]/1 1; THIAMINE 3 mg/1 1; RIBOFLAVIN 3.4 mg/1 1; NIACINAMIDE 20 mg/1 1; PYRIDOXINE HYDROCHLORIDE 20 mg/1 1; FOLIC ACID 1 mg/1 1; POTASSIUM IODIDE 150 mg/1 1; ZINC OXIDE 25 mg/1 1; CUPRIC OXIDE 2 mg/1 1; DOCUSATE SODIUM 50 mg/1 1; CALCIUM CITRATE 124 mg/1 1; DOCONEXENT 250 mg/1 1; ICOSAPENT 0.625 mg/1 1
INACTIVE INGREDIENTS: CROSCARMELLOSE SODIUM; TITANIUM DIOXIDE; MAGNESIUM SILICATE; SHELLAC; ETHYL VANILLIN; VITAMIN A PALMITATE; SUNFLOWER OIL; LECITHIN, SUNFLOWER; ROSEMARY; TOCOPHEROL; ASCORBYL PALMITATE

CitraNatal® DHA

BOXED WARNING

Accidental overdose of iron-containing products is a leading cause of fatal poisoning in children under 6. KEEP THIS PRODUCT OUT OF THE REACH OF CHILDREN. In case of accidental overdose, call a doctor or poison control center immediately.

DESCRIPTION

CitraNatal® DHA is a prescription prenatal/postnatal multi-vitamin/mineral tablet with Ferr-Ease®, a patented dual-iron delivery comprising both a quick release and slow release iron, and a soft gel of an essential fatty acid. The prenatal vitamin is a white, scored, oval multi-vitamin/mineral tablet. The tablet is debossed “CN 1” on one side and is blank on the other. The essential fatty acid DHA soft gel is caramel colored and contains a light yellow to orange semi-solid mixture.

ACTIVE INGREDIENT

Each prenatal tablet contains:
Vitamin C (Ascorbic acid) | 120 mg
Calcium (Calcium citrate) | 124 mg
Iron (Carbonyl iron, ferrous gluconate) | 27 mg
Vitamin D3 (Cholecalciferol) | 400 IU
Vitamin E (dl-alpha tocopheryl acetate) | 30 IU
Thiamin (Vitamin B1) | 3 mg
Riboflavin (Vitamin B2) | 3.4 mg
Niacinamide (Vitamin B3) | 20 mg
Vitamin B6 (Pyridoxine) | 20 mg
Folic Acid | 1 mg
Iodine (Potassium iodide) | 150 mcg
Zinc (Zinc oxide) | 25 mg
Copper (Cupric oxide) | 2 mg
Docusate Sodium | 50 mg

Each DHA soft gel contains:
Docosahexaenoic Acid (DHA, 40% from 625 mg Algal Oil) | 250 mg
Eicosapentaenoic Acid (EPA) | Not more than 0.625 mg
Other ingredients in DHA soft gel: High oleic sunflower oil, sunflower lecithin, rosemary extract, tocopherols, ascorbyl palmitate.

INDICATIONS

CitraNatal® DHA is a multi-vitamin/mineral prescription drug indicated for use in improving the nutritional status of women prior to conception, throughout pregnancy, and in the postnatal period for both lactating and nonlactating mothers.

CONTRAINDICATIONS

This product is contraindicated in patients with a known hypersensitivity to any of the ingredients.

WARNING:
Ingestion of more than 3 grams of omega-3 fatty acids per day has been shown to have potential antithrombotic effects, including an increased bleeding time and INR. Administration of omega-3 fatty acids should be avoided in patients on anticoagulants and in those known to have an inherited or acquired bleeding diathesis.

WARNING:
Folic acid alone is improper therapy in the treatment of pernicious anemia and other megaloblastic anemias where vitamin B12 is deficient.

PRECAUTIONS

Folic acid in doses above 0.1 mg daily may obscure pernicious anemia in that hematologic remission can occur while neurological manifestations progress.

ADVERSE REACTIONS

Allergic sensitization has been reported following both oral and parenteral administration of folic acid.

DOSAGE AND ADMINISTRATION

One tablet and one soft gel daily or as directed by a physician.

STORAGE

Store at 20°C to 25°C (68°F to 77°F), excursions permitted between 15°C and 30°C (between 59°F and 86°F). Brief exposure to temperatures up to 40°C (104°F) may be tolerated provided the mean kinetic temperature does not exceed 25°C (77°F); however, such exposure should be minimalized.

NOTICE: Contact with moisture can discolor or erode the tablet.

HOW SUPPLIED

Six child-resistant blister packs of 5 tablets and 5 soft gels each - NDC 0178-0894-30.

To report a serious adverse event or obtain product information, call (210) 696-8400.

Please consult your health care provider with any dietary concerns.

500243
C01 Rev 002140

DHA soft gels manufactured for:
MISSION PHARMACAL COMPANY
San Antonio, TX USA 78230 1355
Prenatal tablets manufactured by:
MISSION PHARMACAL COMPANY
San Antonio, TX USA 78230 1355

Copyright © 2014 Mission Pharmacal Company.
All rights reserved.

PACKAGE LABEL

Citranatal DHA
Rx Prenatal Vitamin Tablet
and 250 mg DHA Soft Gel
Carton

NDC 0178–0894–30

PACKAGE LABEL

Blister Pack